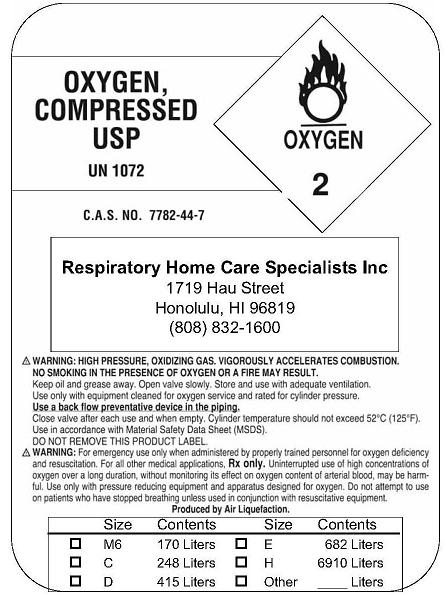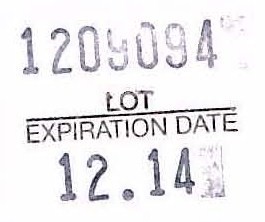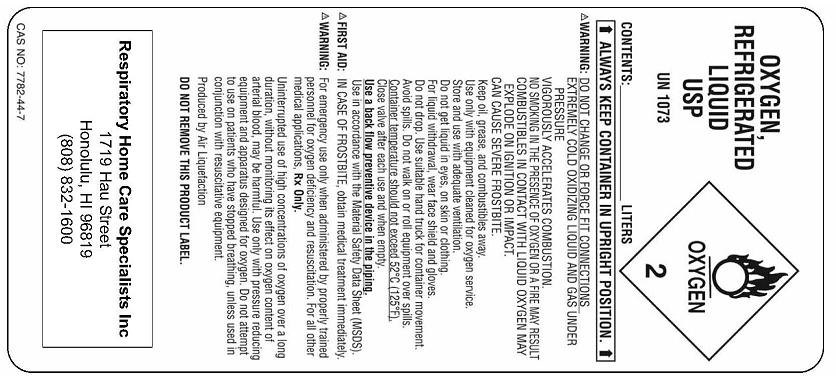 DRUG LABEL: Oxygen
NDC: 62018-001 | Form: GAS
Manufacturer: Respiratory Home Care Specialists, Inc. 
Category: prescription | Type: HUMAN PRESCRIPTION DRUG LABEL
Date: 20091218

ACTIVE INGREDIENTS: Oxygen 99 L/100 L

Oxygen